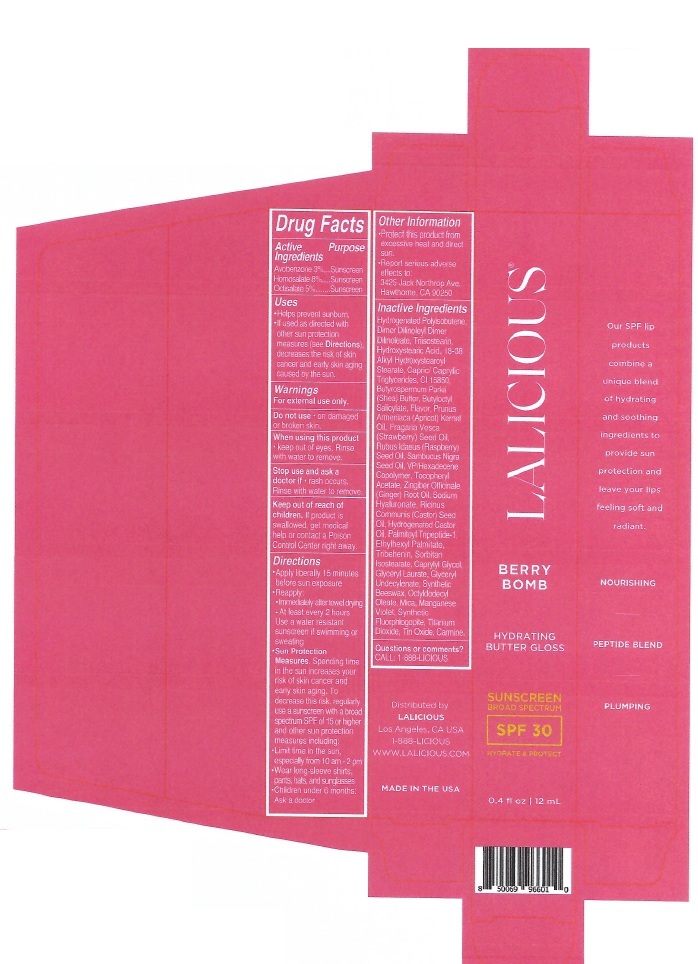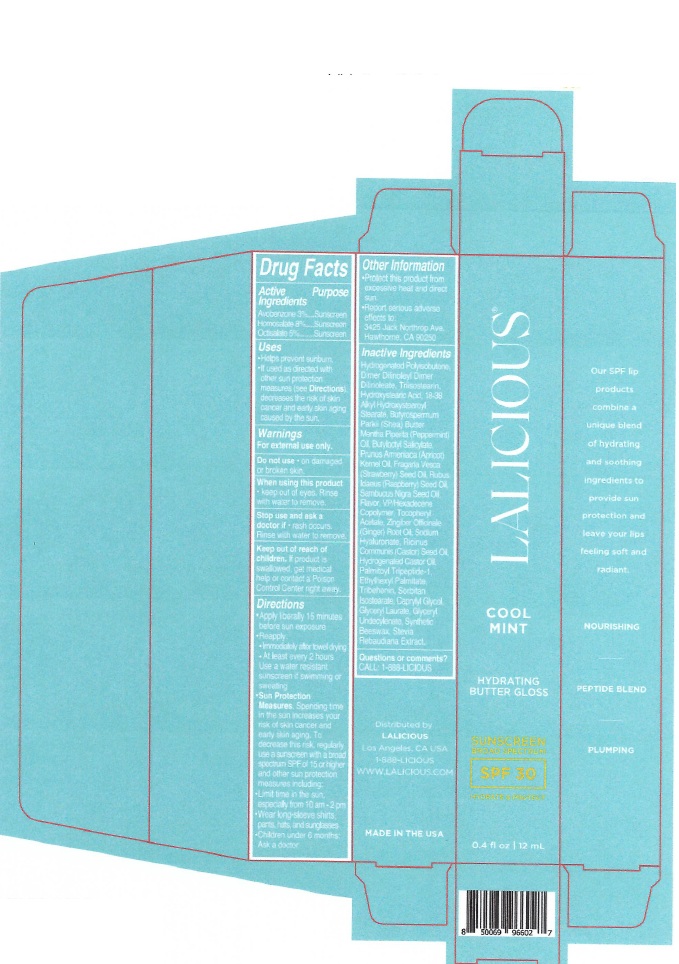 DRUG LABEL: LALICIOUS HYDRATING BUTTER GLOSS SPF 30 BERRY BOMB
NDC: 87042-001 | Form: LIPSTICK
Manufacturer: Lalicious, LLC
Category: otc | Type: HUMAN OTC DRUG LABEL
Date: 20250819

ACTIVE INGREDIENTS: HOMOSALATE 80 mg/1 mL; AVOBENZONE 30 mg/1 mL; OCTISALATE 50 mg/1 mL
INACTIVE INGREDIENTS: .ALPHA.-TOCOPHEROL ACETATE; CAPRYLIC/CAPRIC TRIGLYCERIDE; CI 15850; BUTYLOCTYL SALICYLATE; RASPBERRY SEED OIL; VP/HEXADECENE COPOLYMER; SODIUM HYALURONATE; CASTOR OIL; HYDROGENATED CASTOR OIL; TRIBEHENIN; SORBITAN ISOSTEARATE; GLYCERYL LAURATE; OCTYLDODECYL OLEATE; MANGANESE VIOLET; TITANIUM DIOXIDE; TIN OXIDE; ZINGIBER OFFICINALE (GINGER) ROOT OIL; ETHYLHEXYL PALMITATE; PALMITOYL TRIPEPTIDE-1; CAPRYLYL GLYCOL; SYNTHETIC BEESWAX; C18-38 ALKYL HYDROXYSTEAROYL STEARATE; SAMBUCUS NIGRA SEED OIL; HYDROGENATED POLYISOBUTENE (450 MW); CI 75470; TRIISOSTEARIN; APRICOT KERNEL OIL; HYDROXYSTEARIC ACID; STRAWBERRY SEED OIL; SHEA BUTTER; DIMER DILINOLEYL DIMER DILINOLEATE; MICA; MAGNESIUM POTASSIUM ALUMINOSILICATE FLUORIDE

LALICIOUS HYDRATING BUTTER GLOSS SPF 30

Active Ingredients

Avobenzone 3%

Homosalate 8%

Octisalate 5%

Purpose

Sunscreen

Uses

- Helps prevent sunburn.
- If used as directed with other sun protection measures (see Directions), decreases the risk of skin cancer and early skin aging caused by the sun

Warnings

For external use only.

Do not use

- on damaged or broken skin.

When using this product

- keep out of eyes. Rinse with water to remove.

Stop use and ask a doctor if

- rash occurs. Rinse with water to remove.

Keep out of reach of children.

If product is swallowed, get medical help or contact a Poison Control Center right away.

Directions

- Apply liberally 15 minutes before sun exposure
- Reapply:
- Immediately after towel drying
- At least every 2 hours
- Use a water resistant sunscreen if swimming or sweating
- Sun Protection Measures. Spending time in the sun increases your risk of skin cancer and early skin aging. To decrease this risk, regularly use a sunscreen with a broad spectrum SPF of 15 or higher and other sun protection measures including:
- Limit time in the sun, expecially from 10 am - 2 pm
- Wear long-sleeve shirts, pants, hats, and sunglasses
- Children under 6 months: Ask a doctor

Other Information

- Protect this product from excessive heat and direct sun.
- Report serious adverse effects to: 3425 Jack Northrop Ave. Hawthorne, CA 90250

Inactive Ingredients

Berry Bomb

Hydrogenated Polyisobutene, Dimer Dilinoleyl Dimer Dilinoleate, Triisostearin, Hydroxystearic Acid, C18-38 Alkyl Hydroxystearoyl Stearate, Capric/Caprylic Triglycerides, CI 15850, Butyrospermum Parkii (Shea) Butter, Butyloctyl Salicylate, Flavor, Prunus Armeniaca (Apricot) Kernel Oil, Fragaria Vesca (Strawberry) Seed Oil, Rubus Idaeus (Raspberry) Seed Oil, Sambucus Nigra Seed Oil, VP/Hexadecene Copolymer, Tocopheryl Acetate, Zingiber Officinale (Ginger) Root Oil, Sodium Hyaluronate, Ricinus Communis (Castor) Seed Oil, Hydrogenated Castor Oil, Palmitoyl Tripeptide-1, Ethylhexyl Palmitate, Tribehenin, Sorbitan Isostearate, Caprylyl Glycol, Glyceryl Laurate, Glyceryl Undecylenate, Synthetic Beeswax, Octyldodecyl Oleate, Mica, Manganese Violet, Synthetic Fluorphlogopite, Titanium Dioxide, Tin Oxide, Carmine.

Cool Mint

Hydrogenated Polyisobutene, Dimer Dilinoleyl Dimer Dilinoleate, Triisostearin, Hydroxystearic Acid, C18-38 Alkyl Hydroxystearoyl Stearate, Butyrospermum Parkii (Shea) Butter, Mentha Piperita (Peppermint) Oil, Butyloctyl Salicylate, Prunus Armeniaca (Apricot) Kernel Oil, Fragaria Vesca (Strawberry) Seed Oil, Rubus Idaeus (Raspberry) Seed Oil, Sambucus Nigra Seed Oil, Flavor, VP/Hexadecene Copolymer, Tocopheryl Acetate, Zingiber Officinale (Ginger) Root Oil, Sodium Hyaluronate, Ricinus Communis (Castor) Seed Oil, Hydrogenated Castor Oil, Palmitoyl Tripeptide-1, Ethylhexyl Palmitate, Tribehenin, Sorbitan Isostearate, Caprylyl Glycol, Glyceryl Laurate, Glyceryl Undecylenate, Synthetic Beeswax, Stevia Rebaudiana Extract.

Questions or comments?

CALL 1-888-LICIOUS